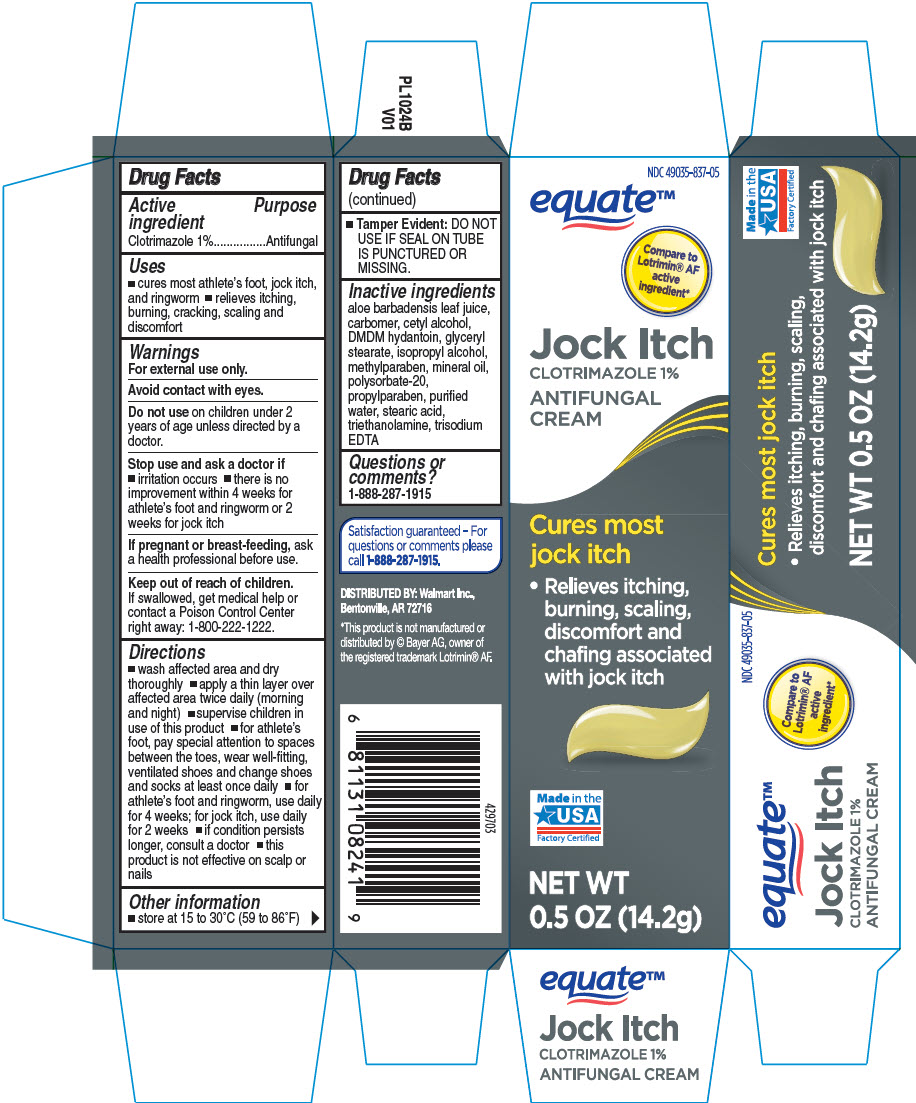 DRUG LABEL: Jock Itch
NDC: 49035-837 | Form: CREAM
Manufacturer: WalMart
Category: otc | Type: HUMAN OTC DRUG LABEL
Date: 20260129

ACTIVE INGREDIENTS: CLOTRIMAZOLE 0.01 g/1 g
INACTIVE INGREDIENTS: ALOE VERA LEAF; BENZYL ALCOHOL; CETOSTEARYL ALCOHOL; CETYL ESTERS WAX; OCTYLDODECANOL; POLYSORBATE 60; SORBITAN MONOSTEARATE; .ALPHA.-TOCOPHEROL ACETATE, DL-; WATER

Jock Itch
Clotrimazole USP 1% Antifungal Cream

Drug Facts

Active ingredient

Clotrimazole 1%

Purpose

Antifungal

Uses

- cures most athlete's foot, jock itch, and ringworm
- relieves itching, burning, cracking, scaling and discomfort

Warnings

For external use only.

Avoid contact with eyes.

Do not use on children under 2 years of age unless directed by a doctor.

Stop use and ask a doctor if

- irritation occurs
- there is no improvement within 4 weeks for athlete's foot and ringworm or 2 weeks for jock itch

PREGNANCY OR BREAST FEEDING

If pregnant or breast-feeding, ask a health professional before use.

Keep out of reach of children.

If swallowed, get medical help or contact a Poison Control Center right away: 800-222-1222.

Directions

- wash affected area and dry thoroughly
- apply a thin layer over affected area twice daily (morning and night)
- supervise children in use of this product
- for athlete's foot, pay special attention to spaces between the toes, wear well-fitting, ventilated shoes and change shoes and socks at least once daily
- for athlete's foot and ringworm, use daily for 4 weeks; for jock itch, use daily for 2 weeks
- if condition persists longer, consult a doctor
- this product is not effective on scalp or nails

Other information

- store at 15 to 30°C (59 to 86°F)
- Tamper Evident: DO NOT USE IF SEAL ON TUBE IS PUNCTURED OR MISSING.

Inactive ingredient

aloe barbadensis leaf juice, carbomer, cetyl alcohol, DMDM hydantoin, glyceryl stearate, isopropyl alcohol, methylparaben, mineral oil, polysorbate-20, propylparaben, purified water, stearic acid, triethanolamine, trisodium EDTA

Questions or comments?

1-888-287-1915

DISTRIBUTED BY: Wal-Mart Stores, Inc.,
Bentonville, AR 72716

PRINCIPAL DISPLAY PANEL - 14.2 g Tube Carton

NDC 49035-837-05

equate™

Compare to
Lotrimin® AF
active
ingredient*

Jock Itch
CLOTRIMAZOLE 1%

ANTIFUNGAL
CREAM

Cures most
jock itch

- Relieves itching,
  burning, scaling,
  discomfort and
  chafing associated
  with jock itch

Made in the
USA
Factory Certified

NET WT
0.5 OZ (14.2g)